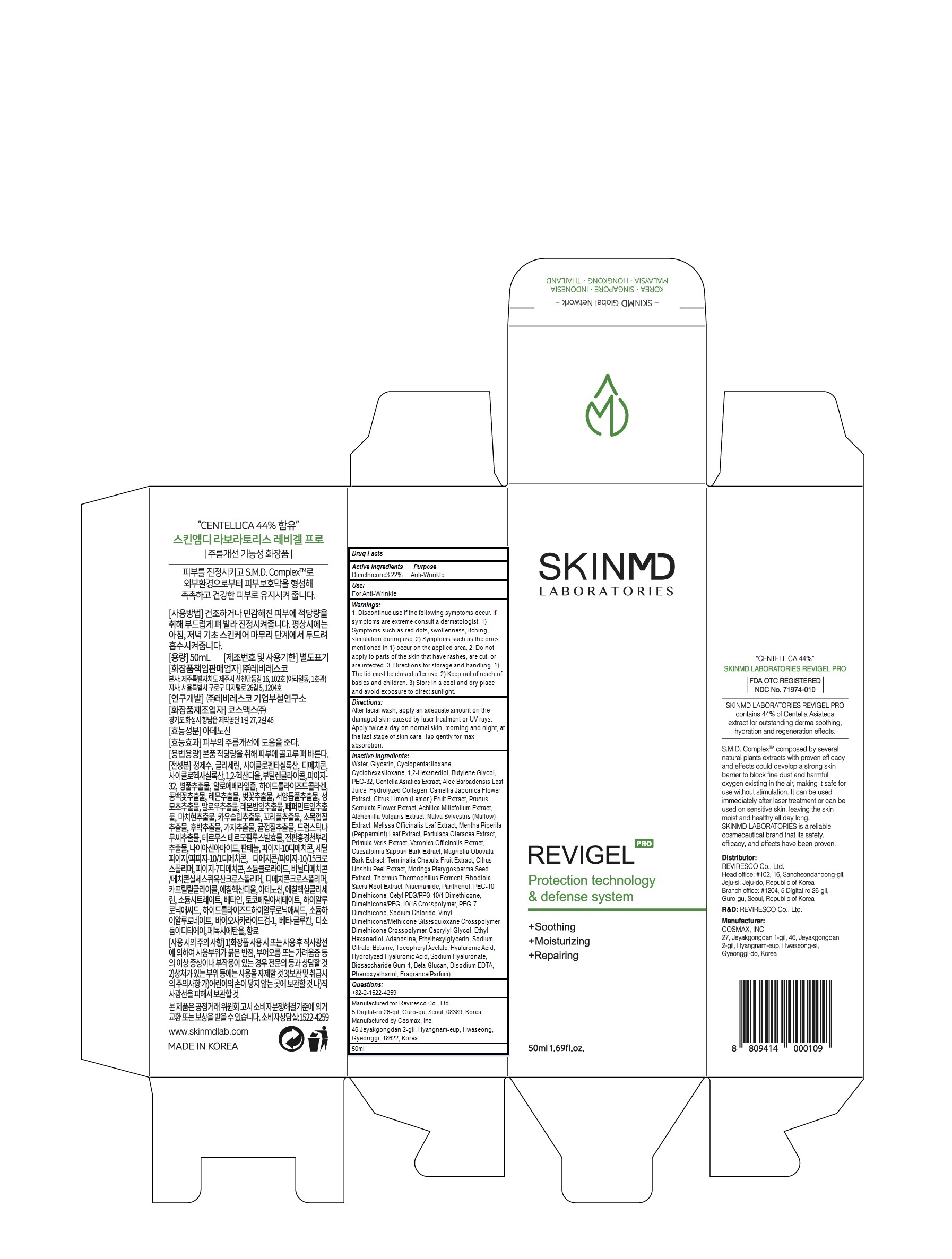 DRUG LABEL: SKINMD LABORATORIES REVIGE L
NDC: 71974-010 | Form: GEL
Manufacturer: Reviresco Co., Ltd.
Category: otc | Type: HUMAN OTC DRUG LABEL
Date: 20191224

ACTIVE INGREDIENTS: Dimethicone 1.61 g/50 mL
INACTIVE INGREDIENTS: Water; Glycerin

ACTIVE INGREDIENT

Active ingredients: Dimethicone 3.22%

INACTIVE INGREDIENT

Inactive ingredients:

Water, Glycerin, Cyclopentasiloxane, Cyclohexasiloxane, 1,2-Hexanediol, Butylene Glycol, PEG-32, Centella Asiatica Extract, Aloe Barbadensis Leaf Juice, Hydrolyzed Collagen, Camellia Japonica Flower Extract, Citrus Limon (Lemon) Fruit Extract, Prunus Serrulata Flower Extract, Achillea Millefolium Extract, Alchemilla Vulgaris Extract, Malva Sylvestris (Mallow) Extract, Melissa Officinalis Leaf Extract, Mentha Piperita (Peppermint) Leaf Extract, Portulaca Oleracea Extract, Primula Veris Extract, Veronica Officinalis Extract, Caesalpinia Sappan Bark Extract, Magnolia Obovata Bark Extract, Terminalia Chebula Fruit Extract, Citrus Unshiu Peel Extract, Moringa Pterygosperma Seed Extract, Thermus Thermophillus Ferment, Rhodiola Sacra Root Extract, Niacinamide, Panthenol, PEG-10 Dimethicone, Cetyl PEG/PPG-10/1 Dimethicone, Dimethicone/PEG-10/15 Crosspolymer, PEG-7 Dimethicone, Sodium Chloride, Vinyl Dimethicone/Methicone Silsesquioxane Crosspolymer, Dimethicone Crosspolymer, Caprylyl Glycol, Ethyl Hexanediol, Adenosine, Ethylhexylglycerin, Sodium Citrate, Betaine, Tocopheryl Acetate, Hyaluronic Acid, Hydrolyzed Hyaluronic Acid, Sodium Hyaluronate, Biosaccharide Gum-1, Beta-Glucan, Disodium EDTA, Phenoxyethanol, Fragrance(Parfum)

PURPOSE

Purpose: Anti-Wrinkle

WARNINGS

1. Discontinue use if the following symptoms occur. If symptoms are extreme consult a dermatologist. 1) Symptoms such as red dots, swollenness, itching, stimulation during use. 2) Symptoms such as the ones mentioned in 1) occur on the applied area. 2. Do not apply to parts of the skin that have rashes, are cut, or are infected. 3. Directions for storage and handling. 1) The lid must be closed after use. 2) Keep out of reach of babies and children. 3) Store in a cool and dry place and avoid exposure to direct sunlight.

KEEP OUT OF REACH OF CHILDREN

Keep out of reach of babies and children.

Uses

Uses: For Anti-Wrinkle

Directions

After facial wash, apply an adequate amount on the damaged skin caused by laser treatment or UV rays. Apply twice a day on normal skin, morning and night, at the last stage of skin care. Tap gently for max absorption.